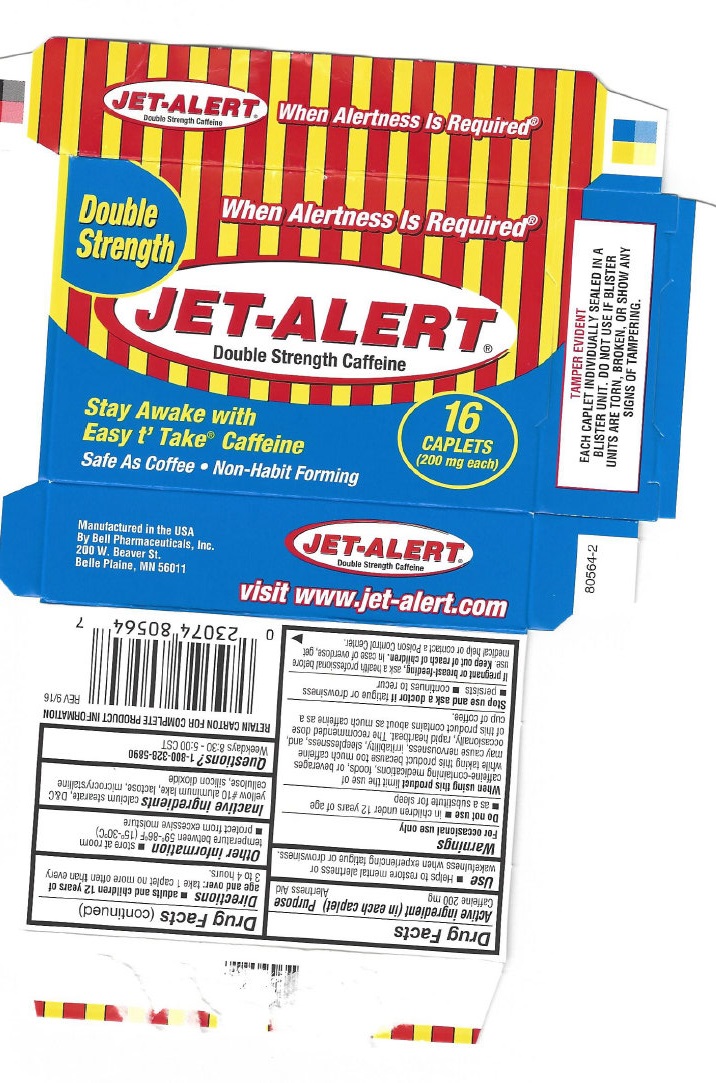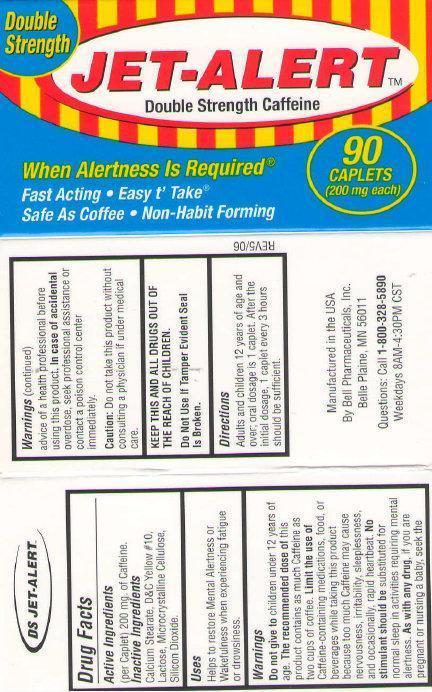 DRUG LABEL: JET ALERT Double Strength
NDC: 15579-200 | Form: TABLET, COATED
Manufacturer: Bell Pharmaceuticals, Inc
Category: otc | Type: HUMAN OTC DRUG LABEL
Date: 20231215

ACTIVE INGREDIENTS: CAFFEINE 200 mg/1 1
INACTIVE INGREDIENTS: CALCIUM STEARATE; D&C YELLOW NO. 10; LACTOSE; CELLULOSE, MICROCRYSTALLINE; SILICON DIOXIDE

JET-ALERT Double Strength

Active ingredient (per caplet)

Caffeine 200 mg

Purpose

Alertness Aid

Uses

Helps restore mental alertness or wakefulness when experiencing fatigue or drowsiness

Warnings

children under 12 years of age. this product contains about as much caffeine as two cup of coffee. caffeine-containing medications, foods, or beverages while taking this product because too much caffeine may cause nervousness, irritability, sleeplessness, and, occasionally, rapid heart beat. No stimulant should be substituted for normal sleep in activities requiring mental alertness. Do not give to The recommended dose of Limit the use of

PREGNANCY OR BREAST FEEDING

As with any drug, if you are pregnant or nursing a baby, seek the advice of a health professional before using this product.

Caution:

Do not take this product without consulting a physician if under medical care.

KEEP OUT OF REACH OF CHILDREN

KEEP THIS AND ALL DRUGS OUT OF REACH OF CHILDREN.

Directions

Adults and children 12 years of age and over: oral dosage is 1 caplet. After the initial dosage, 1 caplet every 3 hours should be sufficient.

Questions:

Call 1-800-328-5890

Weekdays 8AM-4:30PM CST

Inactive ingredients

Calcium Stearate, D&C Yellow #10, Lactose, microcrystalline cellulose, Silicon Dioxide.

Manufactured in the USA

By Bell Pharmaceutucals, Inc.

Belle Plaine, MN 56011

DO NOT USE IF TAMPER-EVIDENT SEAL IS BROKEN